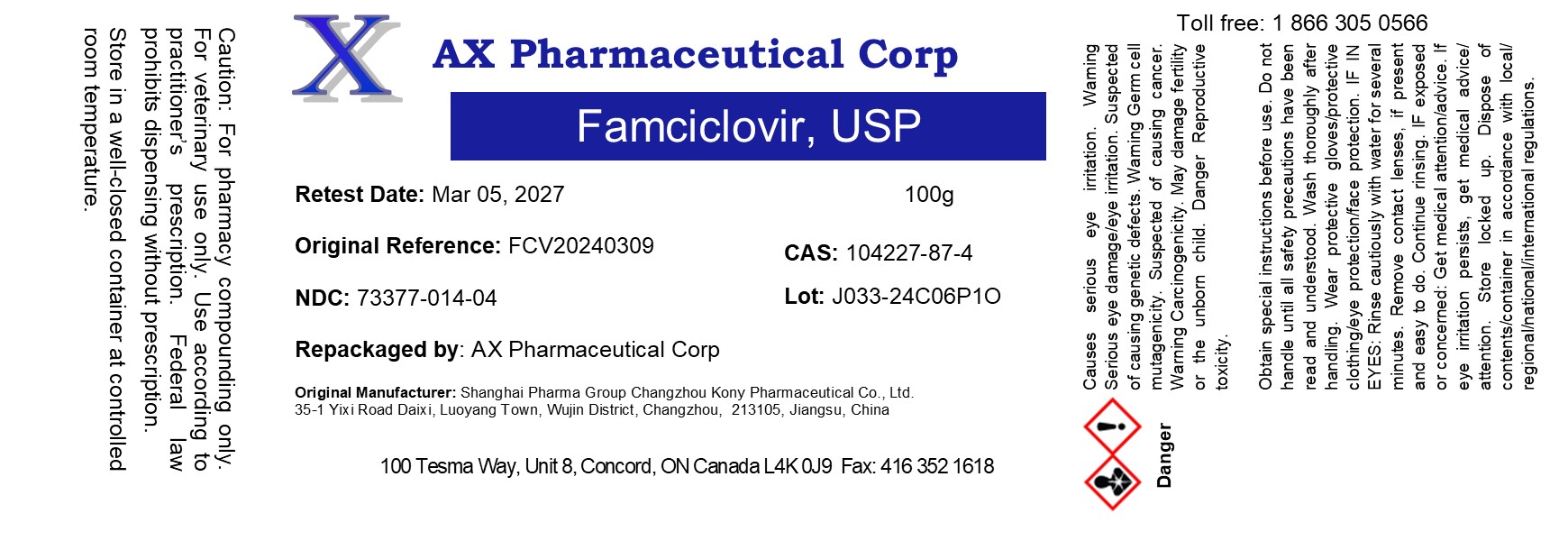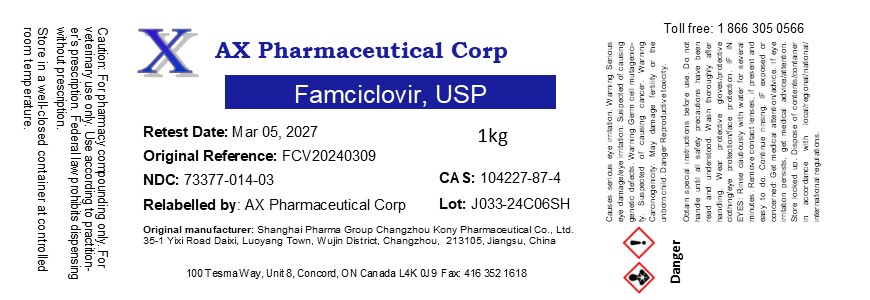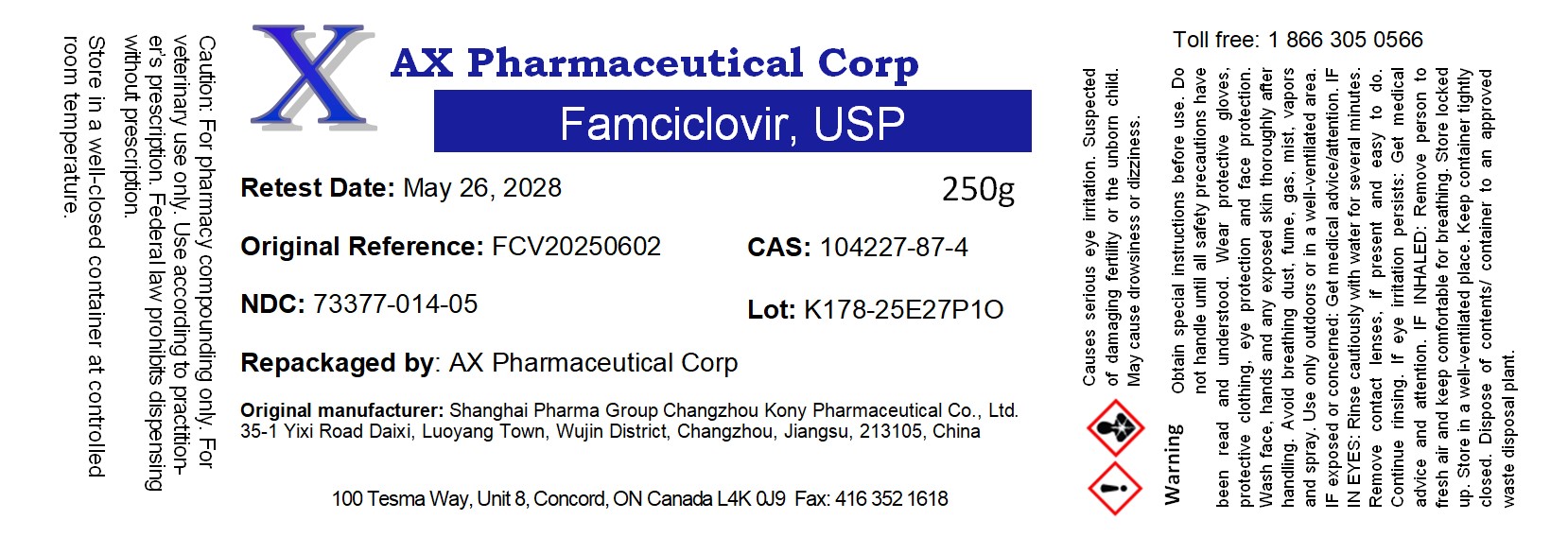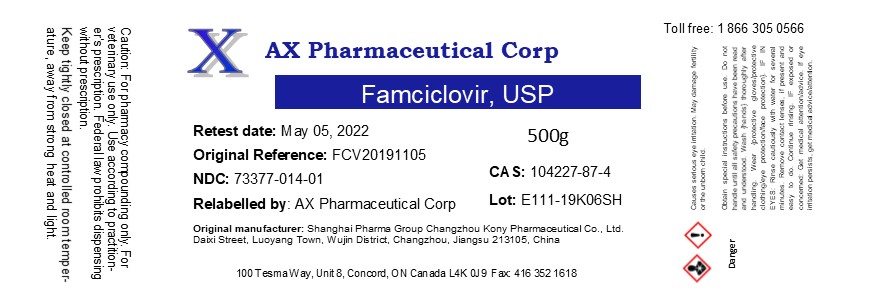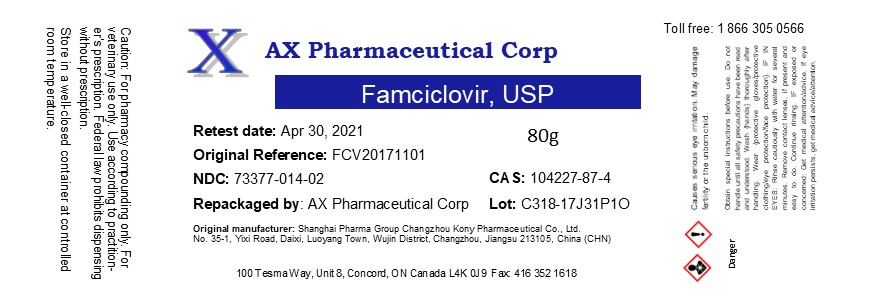 DRUG LABEL: Famciclovir
NDC: 73377-014 | Form: POWDER
Manufacturer: AX Pharmaceutical Corp
Category: other | Type: BULK INGREDIENT - ANIMAL DRUG
Date: 20250903

ACTIVE INGREDIENTS: FAMCICLOVIR 1 g/1 g

Famciclovir